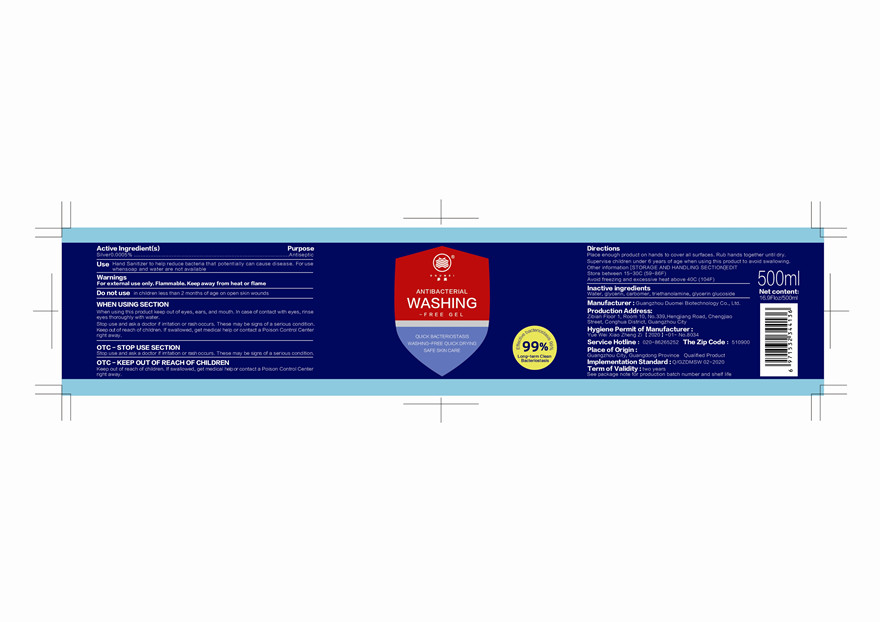 DRUG LABEL: ANTIBACTERIAL  WASHING FREE
NDC: 75238-001 | Form: GEL
Manufacturer: Guangzhou Duomei Biotechnology Co., Ltd.
Category: otc | Type: HUMAN OTC DRUG LABEL
Date: 20200514

ACTIVE INGREDIENTS: SILVER 0.0005 g/100 g
INACTIVE INGREDIENTS: TROLAMINE; GLYCERIN; WATER; CARBOMER HOMOPOLYMER, UNSPECIFIED TYPE

ANTIBACTERIAL WASHING FREE

Active Ingredient(s)

Silver 0.0005%

Purpose

Antiseptic

Use

Hand Sanitizer to help reduce bacteria that potentially can cause disease. For use when soap and water are not available.

Warnings

For external use only.Flammable.Keep away from heat and flame.

Do not use

in children less than 2 months of age on open skin wounds

WHEN USING SECTION

When using this product keep out of eyes,ears,and mouth.In case of contact with eyes, rinse eyes thoroughly with water.

Stop use and ask a doctor if irritation or rash occurs.These may be signs of a serious condition.

Keep out of reach of children.If swallowed, get medical help or contact a Poison Control Center right away.

STOP USE SECTION

Stop use and ask a doctor if irritation or rash occurs.These may be signs of a serious condition.

Keep out of reach of children.If swallowed, get medical help or contact a Poison Control Center right away.

Directions

Place enough product on hands to cover all surfaces. Rub hands together until dry.

Supervise children under 6 years of age when using this product to avoid swallowing.

Other informations

Store between 15-30C(59-86F)

Avoid freezing and excessive heat above 40C(104F)

Inactive ingredients

Water,glycerin,carbomer,triethanolamine,glycerin glucoside.